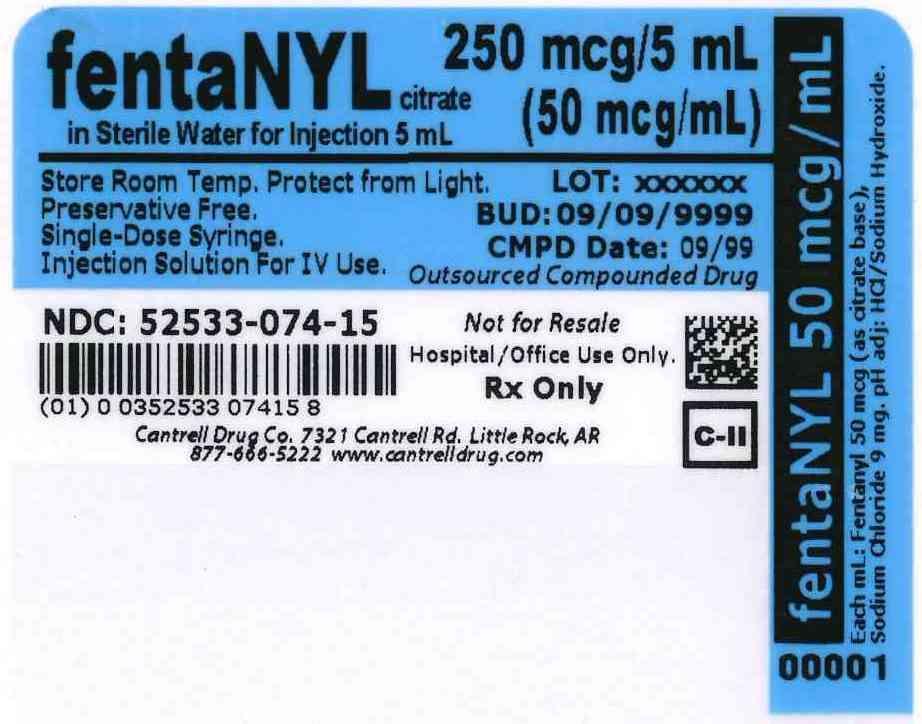 DRUG LABEL: Fentanyl Citrate
NDC: 52533-074 | Form: INJECTION, SOLUTION
Manufacturer: Cantrell Drug Company
Category: prescription | Type: HUMAN PRESCRIPTION DRUG LABEL
Date: 20140502
DEA Schedule: CII

ACTIVE INGREDIENTS: Fentanyl Citrate 50 ug/1 mL
INACTIVE INGREDIENTS: Water; SODIUM CHLORIDE 9 mg/1 mL

Fentanyl Citrate 50 mcg/mL in Sterile Water 5 mL Syringe